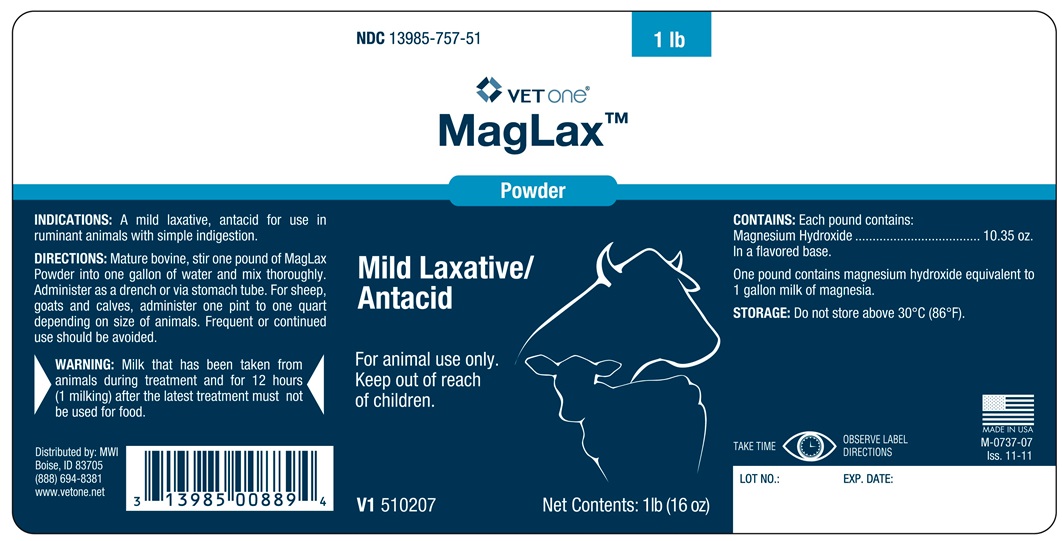 DRUG LABEL: MAGLAX
NDC: 13985-757 | Form: SOLUTION
Manufacturer: MWI Veterinary Supply, Inc.
Category: animal | Type: OTC ANIMAL DRUG LABEL
Date: 20180117

ACTIVE INGREDIENTS: MAGNESIUM HYDROXIDE 293 g/454 g

MagLax Powder

INDICATIONS AND USAGE

Mild Laxative/Antacid

For animal use only.

Keep out of reach of children.

INDICATIONS

A mild laxative, antiacid for use in ruminant animals with simple indigestion.

DIRECTIONS

Mature bovine, stir one pound of MagLax Powder into one gallon of water and mix thoroughly. Administer as a drench or via stomach tube. For sheep, goats and calves, administer one pint to one quart depending on size of animals. Frequent or continued use should be avoided.

WARNING

Milk that has been taken from animals during treatment and for 12 hours (1 milking) after the latest treatment must not be used for food.

CONTAINS

Each pound contains:

Magnesium Hydroxide ........................... 10.35 oz.

In a flavored base.

One pound contains magnesium hydroxide equibalent to 1 gallon milk of magnesia.

STORAGE

Do not store above 30°C (86°F).